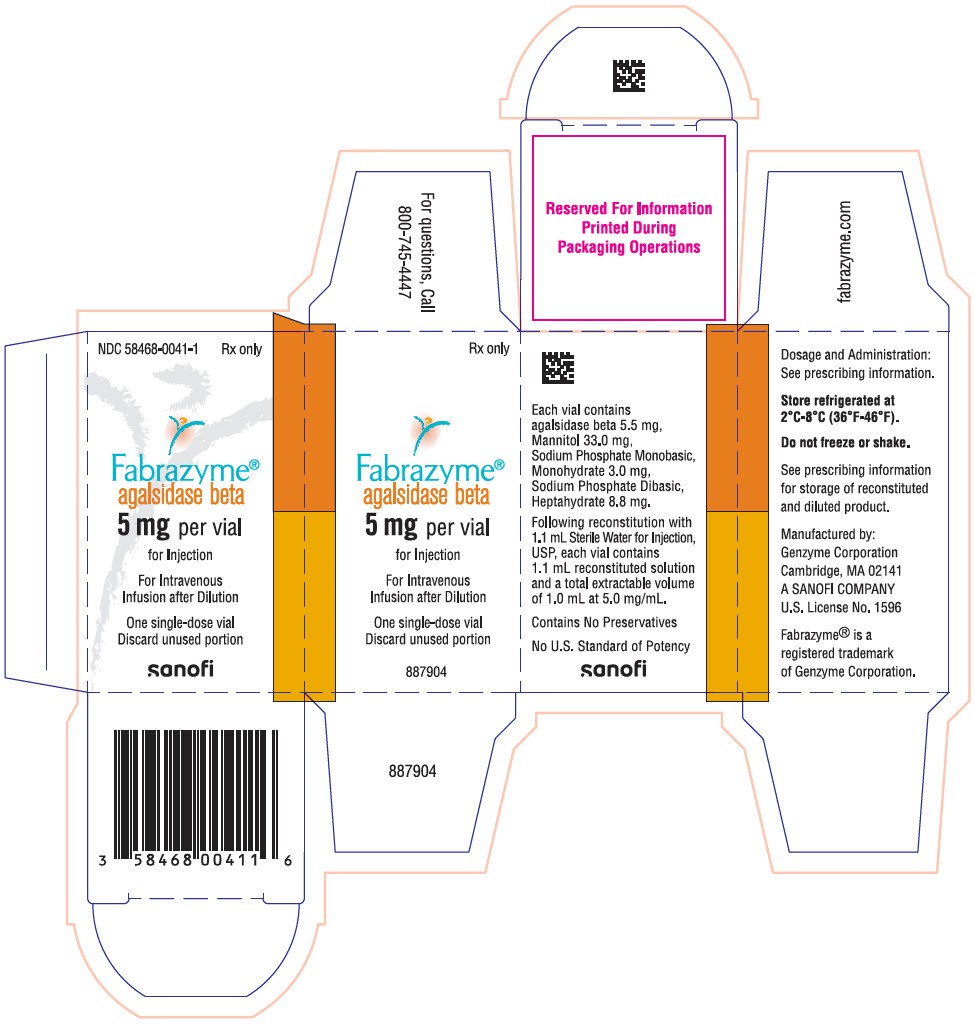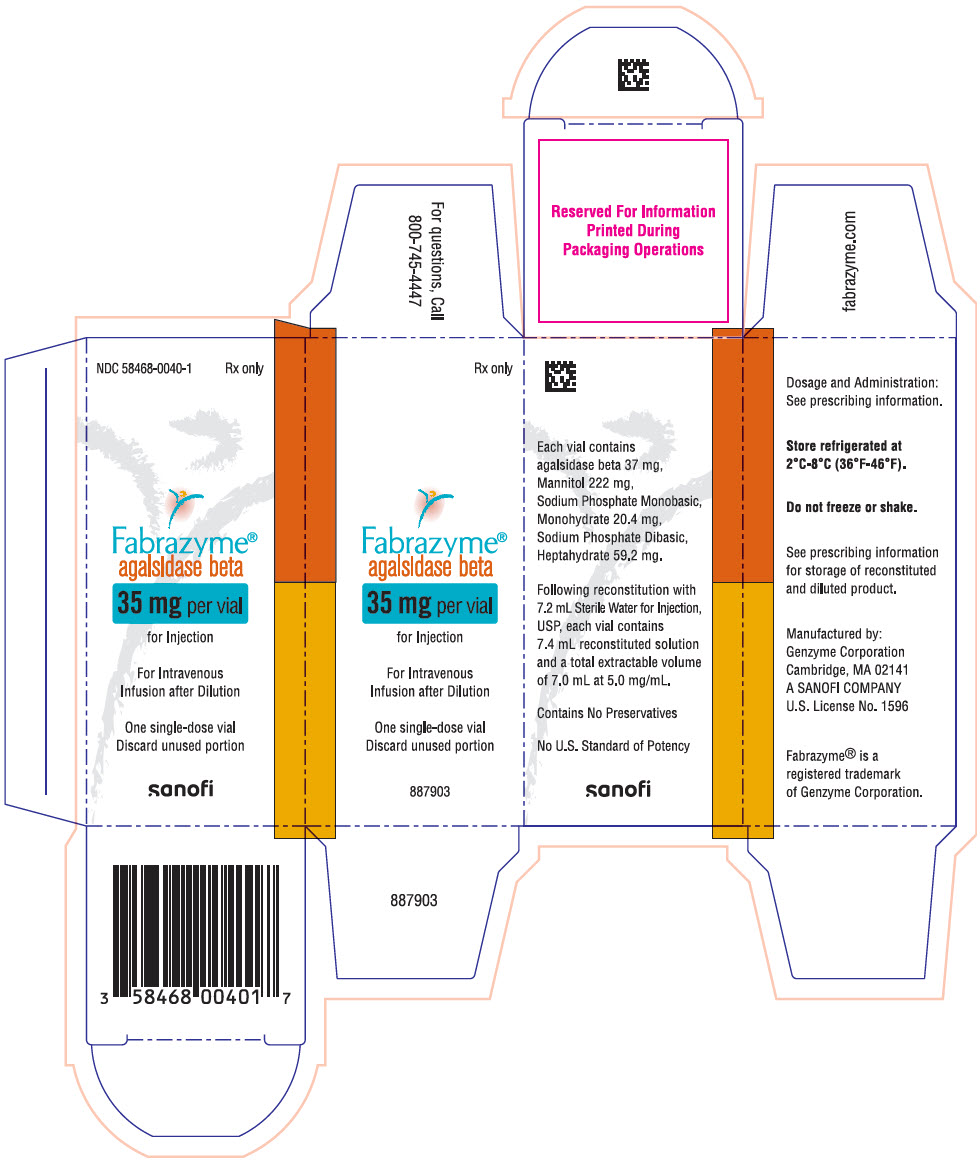 DRUG LABEL: Fabrazyme
NDC: 58468-0041 | Form: INJECTION, POWDER, LYOPHILIZED, FOR SOLUTION
Manufacturer: Genzyme Corporation
Category: prescription | Type: HUMAN PRESCRIPTION DRUG LABEL
Date: 20250822

ACTIVE INGREDIENTS: AGALSIDASE BETA 5 mg/1 mL
INACTIVE INGREDIENTS: MANNITOL 33 mg/1 mL; SODIUM PHOSPHATE, MONOBASIC, MONOHYDRATE 3 mg/1 mL; SODIUM PHOSPHATE, DIBASIC, HEPTAHYDRATE 8.8 mg/1 mL

HIGHLIGHTS OF PRESCRIBING INFORMATION

These highlights do not include all the information needed to use FABRAZYME® safely and effectively. See full prescribing information for FABRAZYME®.
FABRAZYME® (agalsidase beta) for injection, for intravenous use
Initial U.S. Approval: 2003

WARNING: HYPERSENSITIVITY REACTIONS INCLUDING ANAPHYLAXIS

See full prescribing information for complete boxed warning

- Anaphylaxis has occurred during the early course of enzyme replacement therapy and after extended duration of therapy.
- Initiate FABRAZYME in a healthcare setting with appropriate medical monitoring and support measures, including access to cardiopulmonary resuscitation equipment.
- If a severe hypersensitivity reaction (e.g., anaphylaxis) occurs, discontinue FABRAZYME and immediately initiate appropriate medical treatment, including use of epinephrine. (5.1)

RECENT MAJOR CHANGES

Boxed Warning | XX/2024
Dosage and Administration (2.1) | XX/2024
Warnings and Precautions (5.1) | 2/2024

1 INDICATIONS AND USAGE

FABRAZYME is a hydrolytic lysosomal neutral glycosphingolipid-specific enzyme indicated for the treatment of adult and pediatric patients 2 years of age and older with confirmed Fabry disease. (1)

2 DOSAGE AND ADMINISTRATION

- Administration of FABRAZYME should be supervised by a healthcare provider knowledgeable in the management of hypersensitivity reactions including anaphylaxis. (2.1)
- The recommended dosage is 1 mg/kg body weight given every two weeks as an intravenous infusion. (2.2)
- See the full prescribing information for rechallenge, preparation, storage, and administration instructions. (2.3, 2.4, 2.5, 2.6)

3 DOSAGE FORMS AND STRENGTHS

For injection: 5 mg or 35 mg of agalsidase beta as a lyophilized cake or powder in a single-dose vial for reconstitution. (3)

4 CONTRAINDICATIONS

None. (4)

5 WARNINGS AND PRECAUTIONS

- Infusion-Associated Reactions: If a severe infusion-associated reaction occurs, discontinue FABRAZYME immediately and initiate appropriate medical treatment. (5.2)

6 ADVERSE REACTIONS

Most common adverse reactions (≥20%) are: upper respiratory tract infection, chills, pyrexia, headache, cough, paresthesia, fatigue, peripheral edema, dizziness, and rash. (6.1)

To report SUSPECTED ADVERSE REACTIONS, contact Genzyme at 1-800-633-1610 or FDA at 1-800-FDA-1088 or www.fda.gov/medwatch.

FULL PRESCRIBING INFORMATION

WARNING: HYPERSENSITIVITY REACTIONS INCLUDING ANAPHYLAXIS

Patients treated with enzyme replacement therapies have experienced life-threatening hypersensitivity reactions, including anaphylaxis. Anaphylaxis has occurred during the early course of enzyme replacement therapy and after extended duration of therapy. Initiate FABRAZYME in a healthcare setting with appropriate medical monitoring and support measures, including access to cardiopulmonary resuscitation equipment. If a severe hypersensitivity reaction (e.g., anaphylaxis) occurs, discontinue FABRAZYME and immediately initiate appropriate medical treatment, including use of epinephrine. Inform patients of the symptoms of life-threatening hypersensitivity reactions, including anaphylaxis and to seek immediate medical care should symptoms occur. [see Warnings and Precautions (5.1)].

1 INDICATIONS AND USAGE

FABRAZYME® is indicated for the treatment of adult and pediatric patients 2 years of age and older with confirmed Fabry disease.

2 DOSAGE AND ADMINISTRATION

2.1 Recommendations Prior to FABRAZYME Treatment

- Administration of FABRAZYME should be supervised by a healthcare provider knowledgeable in the management of hypersensitivity reactions including anaphylaxis [see Warnings and Precautions (5.1)].
- Initiate FABRAZYME in a healthcare setting with appropriate medical monitoring and support measures, including access to cardiopulmonary resuscitation equipment [see Warnings and Precautions (5.1)].
- Prior to FABRAZYME administration, consider pretreating with antihistamines, antipyretics, and/or corticosteroids [see Warnings and Precautions (5.1, 5.2)].
- FABRAZYME must be reconstituted and diluted prior to use [see Dosage and Administration (2.4)]

2.2 Recommended Dosage and Administration

- The recommended dosage of FABRAZYME is 1 mg/kg body weight infused every two weeks as an intravenous infusion.
- The initial recommended infusion rate is 0.25 mg/min (15 mg/hour) [see Dosage and Administration (2.6)].

2.3 Rechallenge Instructions

Patients who have had a positive skin test to FABRAZYME or who have tested positive for anti-FABRAZYME IgE may be successfully rechallenged with FABRAZYME. The initial rechallenge administration should be a low dose at a lower infusion rate, e.g., one-half the therapeutic dose (0.5 mg/kg) at 1/25th of the initial standard recommended rate (0.01 mg/min or 0.6 mg/hr). Once a patient tolerates the infusion, the dose may be increased to reach the approved dose of 1 mg/kg and the infusion rate may be increased by slowly titrating upwards (doubled every 30 minutes up to a maximum rate of 0.25 mg/minute), as tolerated [see Adverse Reactions (6.2)].

2.4 Preparation Instructions

Use aseptic technique during preparation. Reconstitute and dilute FABRAZYME in the following manner:

Reconstitution Instructions

1. Determine the number of 35 mg and 5 mg FABRAZYME vials to be reconstituted based on actual body weight (kg) and the recommended dose [see Dosage and Administration (2.2)].
2. Remove the required number of 35 mg and 5 mg FABRAZYME vials from the refrigerator and allow the vials to sit for approximately 30 minutes at room temperature 20°C to 25°C (68°F to 77°F) before use.
3. Reconstitute each vial by directing the diluent down the inside wall of each vial then gently tilt and roll each vial. Use the following volumes for reconstitution:
  - 7.2 mL of FABRAZYME Sterile Water for Injection into the 35 mg vial. Total extractable amount per vial is 35 mg, 7 mL.
  - 1.1 mL of Sterile Water for Injection into the 5 mg vial. Total extractable amount per vial is 5 mg, 1 mL.
4. Each reconstituted vial will yield a concentration of 5 mg/mL of agalsidase beta.
5. Do not shake or agitate the product.
6. Visually inspect the reconstituted solution in the vials for particulate matter and discoloration. The reconstituted solution should be clear and colorless. Discard if visible particulate matter is present or the solution is discolored.

Dilution Instructions

7. Select an appropriate size 0.9% Sodium Chloride Injection infusion bag and prepare by removing a volume equal to the required FABRAZYME volume to achieve a total volume per Table 1.
8. Slowly withdraw the required volume of reconstituted solution from the FABRAZYME vial(s). Discard any unused reconstituted solution remaining in the vial.
  Table 1: Total Infusion Volume Based on Patient Weight
  Patient Weight (kg) | Total Volume (mL)
  ≤35 | 50
  35.1 to 70 | 100
  70.1 to 100 | 250
  >100 | 500
9. Gently inject the FABRAZYME reconstituted solution into the port of the 0.9% Sodium Chloride Injection infusion bag. Do not inject into the airspace within the infusion bag.
10. Gently invert the infusion bag to mix the solution. Do not shake or agitate the product. After dilution, the solution will have a final concentration of 0.2 to 0.7 mg/mL of agalsidase beta.

2.5 Storage Instructions for the Reconstituted and Diluted Product

- Dilute the reconstituted solution without delay and use immediately. If immediate use is not possible, the reconstituted and diluted solution may be stored at 2°C to 8°C (36°F to 46°F) for up to 24 hours.

2.6 Administration Instructions

- The initial recommended infusion rate is 0.25 mg/min (15 mg/hour). For patients weighing:
  - 30 kg or more, in the absence of hypersensitivity and/or infusion-associated reactions (IARs), increase the infusion rate in increments of 0.05 to 0.08 mg/min (3 to 5 mg/hour) with each subsequent infusion. The minimum infusion duration is 1.5 hours (based on individual patient tolerability) [see Dosage and Administration (2.6)].
  - Less than 30 kg, the maximum infusion rate is 0.25 mg/minute (15 mg/hour) [see Dosage and Administration (2.6)].
- Do not infuse FABRAZYME in the same intravenous line with other products.
  Administer FABRAZYME using an in-line low protein binding 0.2 µm filter.

3 DOSAGE FORMS AND STRENGTHS

For injection: 5 mg or 35 mg of agalsidase beta as a white to off-white, lyophilized cake or powder in a single-dose vial for reconstitution.

4 CONTRAINDICATIONS

None.

5 WARNINGS AND PRECAUTIONS

5.1 Hypersensitivity Reactions Including Anaphylaxis

Life-threatening hypersensitivity reactions, including anaphylaxis, have been reported in FABRAZYME-treated patients. In clinical trials and postmarketing safety experience with FABRAZYME, approximately 1% of patients developed anaphylaxis or severe hypersensitivity reactions. Reactions have included localized angioedema (including swelling of the face, mouth, and throat), bronchospasm, hypotension, generalized urticaria, dysphagia, rash, dyspnea, flushing, chest discomfort, pruritus, and nasal congestion.

In clinical trials with FABRAZYME, 10 of 238 patients developed IgE antibodies or skin test reactivity specific to FABRAZYME. Two of six patients in the rechallenge study discontinued treatment with FABRAZYME prematurely due to recurrent infusion-associated reactions. Four serious infusion-associated reactions occurred in three patients during FABRAZYME infusions, including bronchospasm, urticaria, hypotension, and development of FABRAZYME-specific antibodies. Other infusion-associated reactions occurring in more than one patient during the study included rigors, hypertension, nausea, vomiting, and pruritus.

Higher incidences of hypersensitivity reactions were observed in adult patients with persistent anti-FABRAZYME antibodies and in adult patients with high antibody titer compared to that in antibody-negative adult patients [see Adverse Reactions (6.2)].

Prior to FABRAZYME administration, consider pretreating with antihistamines, antipyretics, and/or corticosteroids. Administration of FABRAZYME should be supervised by a healthcare provider knowledgeable in the management of hypersensitivity reactions including anaphylaxis. Anaphylaxis has occurred during the early course of enzyme replacement therapy and after extended duration of therapy. Initiate FABRAZYME in a healthcare setting with appropriate medical monitoring and support measures, including access to cardiopulmonary resuscitation equipment.

- If a severe hypersensitivity reaction (e.g., anaphylaxis) occurs, discontinue FABRAZYME and immediately initiate appropriate medical treatment, including use of epinephrine. Consider the risks and benefits of re-administering FABRAZYME following severe hypersensitivity reactions (including anaphylaxis). Inform patients of the symptoms of life-threatening hypersensitivity reactions, including anaphylaxis and to seek immediate medical care should symptoms occur.
  - Consider testing for IgE antibodies in FABRAZYME-treated patients who experienced severe hypersensitivity reactions, including anaphylaxis and consider the risks and benefits of continued treatment in patients with anti-FABRAZYME IgE antibodies. There are no marketed tests for antibodies against FABRAZYME. If testing is warranted, contact Genzyme Corporation at 1-800-745-4447 [see Adverse Reactions (6.2)].
  - Patients who have had a positive skin test to FABRAZYME or who have tested positive for FABRAZYME-specific IgE antibodies have been rechallenged with FABRAZYME using a rechallenge protocol. Rechallenge of these patients should only occur under the direct supervision of qualified personnel with appropriate medical monitoring and support measures readily available [see Dosage and Administration (2.3) and Adverse Reactions (6.2)].

5.2 Infusion-Associated Reactions

In clinical trials of FABRAZYME, 59% of patients experienced infusion-associated reactions (IARs) during FABRAZYME administration, some of which were severe. Infusion-associated reactions are defined as adverse reactions occurring on the same day as the infusion. The incidence of infusion-associated reactions was higher in patients who were positive for anti-FABRAZYME antibodies than in patients who were negative for anti-FABRAZYME antibodies [see Adverse Reactions (6.2)].

Severe infusion-associated reactions experienced by more than one patient in clinical trials of FABRAZYME included chills, vomiting, hypotension, and paresthesia. Other infusion-associated reactions included pyrexia, feeling hot or cold, dyspnea, nausea, flushing, headache, fatigue, pruritus, pain in extremity, hypertension, chest pain, throat tightness, abdominal pain, dizziness, tachycardia, nasal congestion, diarrhea, edema peripheral, myalgia, urticaria, bradycardia, and somnolence [see Adverse Reactions (6.1)].

Prior to FABRAZYME administration, consider pre-treatment with antihistamines, antipyretics, and/or corticosteroids to reduce the risk of infusion-associated reactions (IARs). However, IARs may still occur in patients after receiving pre-treatment. IARs tended to decline in frequency with continued use of FABRAZYME. However, IARs may still occur despite extended duration of FABRAZYME treatment. Appropriate medical monitoring and support measures, including cardiopulmonary resuscitation equipment, should be readily during FABRAZYME administration.

- If a severe IAR occurs, discontinue FABRAZYME immediately and initiate appropriate medical treatment. Consider the risks and benefits of re-administering FABRAZYME following a severe IAR and monitor patients closely upon re-administration of FABRAZYME.
- If a mild or moderate IAR occurs, consider temporarily holding the infusion, slowing the infusion rate, and/or reducing the FABRAZYME dosage.

Patients with advanced Fabry disease may have compromised cardiac function which may predispose them to a higher risk of severe complications from IARs. Closely monitor patients with compromised cardiac function if FABRAZYME is administered to these patients.

6 ADVERSE REACTIONS

The following clinically significant adverse reactions are described elsewhere in labeling:

- Hypersensitivity Reactions Including Anaphylaxis [see Warnings and Precautions (5.1)]
- Infusion-Associated Reactions [see Warnings and Precautions (5.2)]

6.1 Clinical Trials Experience

Because clinical trials are conducted under widely varying conditions, adverse reaction rates observed in clinical trials of a drug cannot be directly compared to rates in the clinical trial of another drug and may not reflect the rates observed in patients in clinical practice.

The data described below reflect exposure of 80 patients, ages 16 to 61 years, to 1 mg/kg FABRAZYME every two weeks in two separate double-blind, placebo-controlled clinical trials, for periods ranging from 1 to 35 months (mean 15.5 months). All 58 patients enrolled in one of the two studies continued into an open-label extension study of FABRAZYME treatment for up to 54 additional months. Patients were treated with antipyretics and antihistamines prior to the infusions.

Most Common Adverse Reactions

Table 2 enumerates adverse reactions that occurred during the double-blind treatment periods of the two placebo-controlled trials (Study 1 and Study 2) [see Clinical Studies (14)]. The most common adverse reactions reported with FABRAZYME were infusion-associated reactions, (FABRAZYME 59% vs placebo 27%) some of which were severe (FABRAZYME 5.0% vs placebo 1.7%). Infusion-associated reactions are defined as adverse reactions occurring on the same day as the infusion.

Common adverse reactions which occurred in ≥20% of patients treated with FABRAZYME and >2.5% compared to placebo are: upper respiratory tract infection, chills, pyrexia, headache, cough, paresthesia, fatigue, peripheral edema, dizziness and rash.

Table 2: Summary of Common Adverse Reactions [Reported at rate of at least 5% in FABRAZYME-treated patients and greater than 2.5% compared to placebo-treated patients.] in Clinical Trials (Study 1 and 2) of Patients with Fabry Disease
Adverse Reaction | FABRAZYME (n=80) % | Placebo (n=60) %
Upper respiratory tract infection [Includes reports of upper respiratory infection, nasal congestion, sinusitis, respiratory tract congestion, and pharyngitis.] | 53 | 42
Chills [Includes reports of chills and feeling cold.] | 49 | 13
Pyrexia | 39 | 22
Headache | 39 | 28
Cough | 33 | 25
Paresthesia | 31 | 18
Fatigue | 24 | 17
Peripheral edema | 21 | 7
Dizziness | 21 | 8
Rash | 20 | 10
Pain in extremity | 19 | 8
Myalgia [Includes reports of myalgia and muscle spasms.] | 18 | 7
Lower respiratory tract infection | 18 | 7
Pain | 16 | 13
Back pain | 16 | 10
Hypertension | 14 | 5
Pruritus | 10 | 3
Tachycardia | 9 | 3
Excoriation | 9 | 2
Increased blood creatinine | 9 | 5
Tinnitus | 8 | 3
Dyspnea | 8 | 2
Fall | 6 | 3
Burning sensation | 6 | 0
Anxiety | 6 | 3
Depression | 6 | 2
Wheezing | 6 | 0
Hypoacusis | 5 | 0
Chest discomfort | 5 | 2
Fungal infection | 5 | 0
Viral infection | 5 | 0
Hot flush | 5 | 0

Most infusion-associated reactions requiring intervention were ameliorated with slowing of the infusion rate, temporarily stopping the infusion, and/or administration of antipyretics, antihistamines, or steroids.

Adverse Reactions in Pediatric Patients

In Study 3, the safety profile of FABRAZYME in pediatric Fabry disease patients, ages 8 to 16 years, was similar to that seen in adults. The most common adverse reactions (>20%) were headache, abdominal pain, pharyngitis, fever, nausea, vomiting, rhinitis, diarrhea, arthralgia, and dizziness [see Use in Specific Populations (8.4) and Clinical Studies (14)].

6.2 Immunogenicity

As with all therapeutic proteins, there is potential for immunogenicity. The detection of antibody formation is highly dependent on the sensitivity and specificity of the assay. Additionally, the observed incidence of antibody (including neutralizing antibody) positivity in an assay may be influenced by several factors including assay methodology, sample handling, timing of sample collection, concomitant medications, and underlying disease. For these reasons, comparison of the incidence of antibodies to FABRAZYME in the studies described below with the incidence of antibodies in other studies or to other agalsidase beta products may be misleading.

Patients with classic Fabry disease in Study 1, Study 2, and extension studies were tested at multiple time points for antibodies to agalsidase beta during the 55 to 58-month period. Approximately 83% (110 of 133) of adult patients receiving agalsidase beta developed antibodies; 77% (102/133) of patients developed neutralizing antibody (NAb) that inhibited in vitro agalsidase beta catalytic activity, which declined over time, and 6% (8/133) of patients developed NAb that inhibited cellular uptake. In pediatric patients with Fabry disease in Study 3 receiving the recommended dose who were 8 to <16 years of age, antibodies to agalsidase beta were detected in approximately 69% (11/16) of patients. Most patients who developed antibodies did so within the first 3 months of treatment. Antibody titers generally declined over time. Approximately 18% of adult patients who developed antibodies became antibody negative by 74 weeks (median time) from the time of seroconversion; however, none of the pediatric patients became antibody negative. Female patients generally had lower incidence of antibodies and lower antibody titers compared to male patients. In Study 5, patients with truncating GLA mutations had higher incidence of antibodies and higher antibody titers compared to patients with nontruncating GLA mutations. Patients with plasma α-galactosidase A activity ≤1.5 nmol/hr/mL had higher incidence of antibodies and higher antibody titers compared to patients with plasma α-galactosidase A activity >1.5 nmol/hr/mL.

In general, over 90% of adult and pediatric patients treated with agalsidase beta achieved and maintained normalization of plasma globotriaosylceramide (GL-3) levels irrespective of developing antibodies to agalsidase beta.

Study 4 was an open-label, rechallenge study to evaluate the safety of FABRAZYME treatment in patients who had a positive skin test to FABRAZYME or who had tested positive for FABRAZYME-specific IgE antibodies. In this study, six adult male patients, who had experienced multiple or recurrent infusion-associated reactions during previous clinical trials of FABRAZYME, were rechallenged with FABRAZYME administered as a graded infusion for up to 52 weeks of treatment. The initial two rechallenge doses of FABRAZYME were administered as a 0.5 mg/kg dose per week at an initial infusion rate of 0.01 mg/min for the first 30 minutes (1/25th the usually recommended maximum infusion rate). The infusion rate was doubled every 30 minutes thereafter, as tolerated, for the remainder of the infusion up to a maximum rate of 0.25 mg/min. If the patient tolerated the infusion, the dose was increased to 1 mg/kg every two weeks and the infusion rate was increased by slow upwards titration [see Dosage and Administration (2.1)]. Pretreatment was not permitted for at least the first 4 infusions in order to allow early recognition of acute systemic hypersensitivity reactions. Four of the six patients treated in this study received at least 26 weeks of FABRAZYME (2 patients received 26 weeks and 2 patients received 52 weeks), and two patients discontinued prematurely due to recurrent infusion-associated reactions [see Warnings and Precautions (5.1, 5.2)].

Testing for IgE antibodies was performed in approximately 60 patients in clinical trials who experienced moderate to severe infusion-associated reactions or in whom mast cell activation was suspected. Seven of these patients tested positive for FABRAZYME-specific IgE antibodies or had a positive skin test to FABRAZYME. Patients who have had a positive skin test to FABRAZYME, or who have tested positive for FABRAZYME-specific IgE antibodies in clinical trials with FABRAZYME have been rechallenged [see Dosage and Administration (2.1) and Warnings and Precautions (5.1, 5.2)].

The incidences of hypersensitivity reactions were 51% (41/80) and 60% (25/42) in adult patients with persistent anti-FABRAZYME antibodies and in adult patients with high antibody titer, respectively, compared to 30% (7/23) in antibody-negative adult patients [see Warnings and Precautions (5.1)].

The incidence of infusion-associated reactions was 76% (84/110) in antibody-positive adult patients compared to 30% (7/23) in antibody-negative adult patients. The incidence of infusion-associated reactions was 46% (5/11) in antibody positive pediatric patients compared to 20% (1/5) in antibody negative pediatric patients [see Warnings and Precautions (5.2)].

6.3 Postmarketing Experience

The following adverse reactions have been identified during postapproval use of FABRAZYME. Because these reactions are reported voluntarily from a population of uncertain size, it is not always possible to reliably estimate their frequency or establish a causal relationship to drug exposure.

- Cardiovascular: cardiorespiratory arrest, cardiac failure, myocardial infarction, palpitations
- Hypersensitivity reactions: anaphylaxis [see Warnings and Precautions (5.1)], localized angioedema (including auricular swelling, eye swelling, dysphagia, lip swelling, edema, pharyngeal edema, face swelling, and swollen tongue), and bronchospasm
- General: hyperhidrosis, asthenia, infusion site reaction
- Lymphatic: lymphadenopathy
- Musculoskeletal: arthralgia
- Neurologic: cerebrovascular accident, hypoesthesia, oral hypoesthesia
- Pulmonary: respiratory failure, hypoxia
- Renal: renal failure
- Vascular: leukocytoclastic vasculitis

8 USE IN SPECIFIC POPULATIONS

8.1 Pregnancy

Risk Summary

Available data from a pregnancy sub-study within the Fabry Disease registry, post-marketing case reports, and case series with FABRAZYME use during pregnancy have not identified a drug-associated risk of major birth defects, miscarriage or other adverse maternal or fetal outcomes (see Data). Reproduction studies performed in rats at doses up to 68 times the human dose have revealed no evidence of effects on embryo-fetal development (see Data).

The background risk of major birth defects and miscarriage for the indicated population is unknown. All pregnancies have a background risk of birth defect, loss or other adverse outcomes. In the U.S. general population, the estimated background risk of major birth defects and miscarriage in clinically recognized pregnancies is 2% to 4% and 15% to 20%, respectively.

Data

Human Data

Available data from a pregnancy sub-study within the Fabry Disease registry, post-marketing case reports, and case series with FABRAZYME use during pregnancy have not identified a drug-associated risk of major birth defects, miscarriage or other adverse maternal or fetal outcomes. In the Fabry Disease registry pregnancy sub-study, 33 pregnancies exposed to FABRAZYME prior to or during pregnancy had a known outcome; 5 were reported as exposed in the first trimester.

Animal Data

The effects of agalsidase beta on embryo-fetal development in rats were evaluated at doses of 3, 10, and 30 mg/kg/day (up to 68 times the human dose of 1 mg/kg every 2 weeks on a body surface area basis) during gestation days 7 to 17. Hepatocellular necrosis consistent with accumulation of test article was evident in maternal livers in the 10 and 30 mg/kg/day groups (23 and 68 times the human dose on a body surface area basis). There were no adverse effects of agalsidase beta on embryo-fetal development in rats.

8.2 Lactation

Risk Summary

The available human data detected small amounts of agalsidase beta in human milk. Available data from the clinical study, global pharmacovigilance database, and published scientific literature are insufficient to determine the effects of FABRAZYME on the breastfed infant or on milk production. The developmental and health benefits of breastfeeding should be considered along with the mother's clinical need for FABRAZYME and any potential adverse effects on the breastfed child from FABRAZYME or from the underlying maternal condition.

8.4 Pediatric Use

The safety and effectiveness of FABRAZYME have been established in pediatric patients based on adequate and well-controlled studies in adults, a single-arm, open-label study in 16 pediatric patients with Fabry disease aged 8 to 16 years, and additional data in 24 patients with Fabry disease aged 2 to 7 years [see Clinical Pharmacology (12.2) and Clinical Studies (14)].

The overall safety profile of FABRAZYME was similar between the pediatric and the adult population [see Adverse Reactions (6.1) and Clinical Studies (14)].

8.5 Geriatric Use

Clinical studies of FABRAZYME did not include sufficient numbers of subjects aged 65 years and older to determine whether they respond differently from younger subjects.

11 DESCRIPTION

Agalsidase beta is a recombinant human α-galactosidase A enzyme with the same amino acid sequence as the native enzyme. Purified agalsidase beta is a homodimeric glycoprotein with a molecular weight of approximately 100 kD. The mature protein is comprised of two subunits of 398 amino acids (approximately 51 kD), each of which contains three N-linked glycosylation sites. The enzyme α-galactosidase A catalyzes the hydrolysis of GL-3 and other α-galactyl-terminated neutral glycosphingolipids, such as galabiosylceramide and blood group B substances to ceramide dihexoside and galactose. The specific activity of agalsidase beta is approximately 70 U/mg (one unit is defined as the amount of activity that results in the hydrolysis of 1 µmole of a synthetic substrate, p-nitrophenyl-α-D-galactopyranoside, per minute under the assay conditions).

Agalsidase beta is produced by recombinant DNA technology in a Chinese hamster ovary mammalian cell expression system.

FABRAZYME (agalsidase beta) for injection is intended for intravenous infusion. It is supplied as a sterile, nonpyrogenic, preservative-free, white to off-white, lyophilized cake or powder for reconstitution with Sterile Water for Injection, USP.

Each 35 mg vial contains 37 mg of agalsidase beta, as well as 222 mg mannitol, 20.4 mg sodium phosphate monobasic monohydrate, and 59.2 mg sodium phosphate dibasic heptahydrate. Following reconstitution as directed, 35 mg of agalsidase beta (7 mL) may be extracted from each 35 mg vial.

Each 5 mg vial contains 5.5 mg of agalsidase beta, as well as 33.0 mg mannitol, 3.0 mg sodium phosphate monobasic monohydrate, and 8.8 mg sodium phosphate dibasic heptahydrate. Following reconstitution as directed, 5 mg of agalsidase beta (1 mL) may be extracted from each 5 mg vial.

12 CLINICAL PHARMACOLOGY

12.1 Mechanism of Action

FABRAZYME (agalsidase beta) provides an exogenous source of α-galactosidase A in Fabry disease patients. Agalsidase beta is internalized and transported into lysosomes where it exerts enzymatic activity and reduces accumulated GL-3.

12.2 Pharmacodynamics

In Study 1, baseline mean values for plasma GL-3 were similar in the FABRAZYME (14.4 µg/mL) and the placebo (14.7 µg/mL) treatment groups. In the FABRAZYME treatment group, all 29 patients experienced normalization of plasma GL-3 levels (≤7.03 µg/mL) and they maintained normal plasma GL-3 levels for up to 60 months of treatment. Follow-up heart and kidney biopsies were assessed at month 54 in only 8 of the 44 patients, which showed sustained GL-3 clearance in the capillary endothelium of the kidney in 8 patients, and sustained GL-3 clearance in the capillary endothelium of the heart in 6 patients. The reduction in tissue GL-3 is summarized in the clinical studies section (Table 4) [see Clinical Studies (14)].

In Study 2, patients in the FABRAZYME treatment group had mean plasma GL-3 levels that decreased from 9.0 µg/mL at baseline (N=49) to 4.8 µg/mL at one year (N=37) and 4.8 µg/mL at two years (N=18). In the placebo group, the mean plasma GL-3 was 9.1 µg/mL at baseline (N=31), 8.8 µg/mL at one year (N=21), and 9.4 µg/mL at two years (N=7).

In Study 3, at baseline, all 14 males had elevated plasma GL-3 levels (i.e., >7.03 µg/mL), whereas the two female patients had normal plasma GL-3 levels. At weeks 24 and 48 of treatment, all 14 males had plasma GL-3 within the normal range. The two female patients' plasma GL-3 levels remained normal through study week 48. Histological evaluation of the capillary endothelium (vasculature), deep vessel endothelium, deep vessel smooth muscle cells, and perineurium of biopsied skin was conducted using histochemistry with light microscopy. Scoring was on a scale of 0 to 3 (0 defined as none; 1 as mild, 2 as moderate, and 3 as severe). At baseline, 12 of the 14 males had GL-3 inclusions present on skin biopsy (scores 1, 2, or 3) and all 12 achieved GL-3 inclusion scores of 0 at weeks 24 and 48 of treatment. The two females had no GL-3 inclusions in skin at baseline.

In Study 5, in an analysis of 24 FABRAZYME-treated pediatric patients with Fabry disease aged 2 to <8 years at FABRAZYME initiation and with elevated plasma GL-3 levels (i.e., >7.03 μg/mL) at baseline, plasma GL-3 levels fell within the normal range (i.e., ≤7.03 μg/mL) in 91% (20/22), 95% (18/19), and 92% (12/13) of patients at 6, 12, and 24 months, respectively.

12.3 Pharmacokinetics

The pharmacokinetics of FABRAZYME in clinical studies with adult and pediatric patients with Fabry disease is summarized in Table 3.

FABRAZYME exhibited nonlinear pharmacokinetics following intravenous infusions at 0.3 (30% of the approved recommended dosage), 1 mg/kg, and 3 mg/kg (3 times the approved recommended dosage) in adult patients. The area under the plasma concentration-time curve (AUCinf) and the maximum plasma concentration (Cmax) increased greater than dose proportional with increasing doses. The AUCinf and Cmax following multiple dose administrations were comparable to their values at the first dose.

In pediatric patients 8 to 16 years of age with body weight ranging from 27 to 65 kg, the AUCinf and Cmax following multiple dose administrations were higher compared to their values at the first dose. The increased plasma concentrations following multiple dose administration in pediatric patients could be due to formation of antidrug antibodies; however, such impact was not observed in adult patients [see Adverse Reactions (6.2) and Use in Specific Populations (8.4)].

Table 3: FABRAZYME Pharmacokinetic Summary
Dose | Regimen | Mean Infusion Length (min) | Infusion number (n=patients) | AUCinf µg min/mL | Cmax µg/mL | Half-life min | CL mL/min/kg | Vss [Vss = volume of distribution at steady state.] mL/kg
Study FB9702-01: Phase 1/2 Study in Adult Patients with Fabry Disease
0.3 mg/kg | q14 days × 5 | 132 | 1 (n=3) | 79 ± 24 | 0.6 ± 0.2 | 92 ± 27 | 4.1 ± 1.2 | 225 ± 62
 |  | 128 | 5 (n=3) | 74 ± 30 | 0.6 ± 0.2 | 78 ± 67 | 4.6 ± 2.2 | 330 ± 231
1 mg/kg | q14 days × 5 | 115 | 1 (n=3) | 496 ± 137 | 5.0 ± 1.1 | 67 ± 12 | 2.1 ± 0.7 | 112 ± 13
 |  | 120 | 5 (n=2) | 466 ± 382 | 4.74 ± 4.3 | 45 ± 3 | 3.2 ± 2.6 | 243 ± 236
3 mg/kg | q14 days × 5 | 129 | 1 (n=2) | 4168 ± 1401 | 29.7 ± 14.6 | 102 ± 4 | 0.8 ± 0.3 | 81 ± 45
 |  | 300 | 5 (n=2) | 4327 ± 2074 | 19.8 ± 5.8 | 87 ± 21 | 0.8 ± 0.4 | 165 ± 80
Study 1: Phase 3 Study in Adult Patients with Fabry Disease
1 mg/kg | q14 days × 11 | 280 | 1–3 (n=11) | 649 ± 226 | 3.5 ± 1.6 | 89 ± 20 | 1.8 ± 0.8 | 120 ± 80
 |  | 280 | 7 (n=11) | 372 ± 223 | 2.1 ± 1.14 | 82 ± 25 | 4.9 ± 5.6 | 570 ± 710
 |  | 300 | 11 (n=11) | 784 ± 521 | 3.5 ± 2.2 | 119 ± 49 | 2.3 ± 2.2 | 280 ± 230
Study 3: Phase 2 Study in Pediatric Patients with Fabry Disease
1 mg/kg | q14 days × 24 | 208 | 1 (n=8–9) | 344 ± 307 | 2.2 ± 1.9 | 86 ± 27 | 5.8 ± 4.6 | 1097 ± 912
 |  | 111 | 12 (n=15) | 1007 ± 688 | 4.9 ± 2.4 | 130 ± 41 | 1.6 ± 1.2 | 292 ± 185
 |  | 108 | 24 (n=9–10) | 1238 ± 547 | 7.1 ± 4.4 | 151 ± 59 | 1.1 ± 0.8 | 247 ± 146
All data reported as the mean ± standard deviation.

13 NONCLINICAL TOXICOLOGY

13.1 Carcinogenesis, Mutagenesis, Impairment of Fertility

There are no animal or human studies to assess the carcinogenic or mutagenic potential of FABRAZYME. A study to evaluate the effects of agalsidase beta on fertility and general reproduction was performed in male and female rats at doses up to 10 mg/kg/day (23 times the human dose, on a body surface area basis). There were no adverse effects of agalsidase beta on fertility and early embryonic development in rats.

14 CLINICAL STUDIES

The safety and efficacy of FABRAZYME were assessed in four clinical studies in patients with Fabry disease and one matched analysis based on data from observational studies.

Study 1 was a randomized, double-blind, placebo-controlled, multinational, multicenter study of 58 patients with Fabry disease (56 males and 2 females), ages 16 to 61 years, all naive to enzyme replacement therapy [see Clinical Pharmacology (12.2)]. Patients were randomized 1:1 to receive either FABRAZYME 1 mg/kg every 2 weeks or placebo for 20 weeks. Patients had a median age of 24 years in the placebo group and 33 years in the FABRAZYME group at baseline. At baseline, all patients had plasma αGAL activity below the detection limit and 79% had leukocyte αGAL activity below the detection limit. The median plasma GL-3 at baseline was 14.4 ng/uL in the placebo group and 14.7 ng/uL in the FABRAZYME group with the overall range of <1.2 to 36 ng/uL. The median eGFR at baseline was 98.5 mL/hr in the placebo group and 83.0 mL/hr in the FABRAZYME group (overall range 24 to 153 mL/hr). All patients were pretreated with acetaminophen and an antihistamine. Oral steroids were an additional option to the pretreatment regimen for patients who exhibited severe or recurrent infusion-associated reactions.

Tissue biopsy specimens (kidney, heart, skin) were evaluated at baseline and at week 20 by light microscopy for the presence and number of GL-3 inclusions using a semi-quantitative methodology. Renal interstitial capillaries were scored based on the number of GL-3 inclusions on a scale of 0 to 3 (0 defined as "nearly none" or "trace," 1 defined as "mild," 2 defined as "moderate," and 3 defined as "severe"). The primary endpoint was the proportion of patients in either group with a renal capillary GL-3 inclusion score of zero at week 20. In the FABRAZYME group, 20 of 29 (69%) patients achieved a score of zero while 0 of 29 placebo-treated patients achieved a score of zero (p<0.001). Similar reductions in GL-3 inclusions were observed in the capillary endothelium of the heart and skin (Table 4). All 58 patients who completed Study 1 were subsequently treated with FABRAZYME 1 mg/kg every two weeks in an open-label extension study. After six months of open-label treatment, most patients with available biopsy data achieved a GL-3 inclusion score of 0 in capillary endothelium (Table 4).

Table 4: Proportion of Patients with Tissue GL-3 Inclusion Score of Zero (Study 1 and open-label treatment)
 | 20 weeks of randomized treatment in Study 1 |  | 6 months of FABRAZYME open-label treatment
 | Placebo (n=29) | FABRAZYME (n=29) | Placebo/FABRAZYME (n=29) [Results reported where biopsies were available.] | FABRAZYME/FABRAZYME (n=29)
Kidney | 0/29 | 20/29 | 24/24 | 23/25
Heart | 1/29 | 21/29 | 13/18 | 19/22
Skin | 1/29 | 29/29 | 25/26 | 26/27

Study 2 was a randomized (2:1 FABRAZYME to placebo), double-blind, placebo-controlled, multinational, multicenter study of 82 patients (72 males and 10 females) with Fabry disease, all naive to enzyme replacement therapy [see Clinical Pharmacology (12.2)]. Of the 82 enrolled patients, 51 and 31 patients were randomized to the FABRAZYME and placebo groups, respectively. Patients were 20 to 72 years of age with a median age of 45 years at baseline, a median age of 36 years at Fabry disease diagnosis, and at a median of 10 years at symptom onset. The median plasma GL-3 at baseline was 9.3 ug/mL in the placebo group and 8.9 ug/mL in the FABRAZYME group with the overall range of 2.8 to 18.9 ug/mL. At baseline, patients had median plasma αGAL activity 1.5 nmol/hour/mL (range: 0 to 1.5), leukocyte αGAL activity 1.8 nmol/hour/mL (range: 0 to 4.0), eGFR 52 mL/min/1.73 m^2 (range: 25 to 113), and protein to creatinine ratio 0.9 mg/mg (range: 0 to 7.3). Patients received either 1 mg/kg FABRAZYME IV or placebo every two weeks for up to 35 months (median follow-up 18.5 months). The primary efficacy endpoint was the time to first occurrence of a clinically significant event (renal, cardiac, or cerebrovascular event, or death). A total of 14 of 51 (28%) FABRAZYME-treated patients and 13 of 31 (42%) placebo-treated patients experienced a clinically significant event (HR 0.57, 95% CI: 0.27, 1.22).

Study 3 (Pediatric Study) was an open-label, single-arm, multinational, multicenter study in 16 pediatric patients with Fabry disease (14 males, 2 females), aged 8 to 16 years (median 12 years) [see Clinical Pharmacology (12.2)]. At baseline, patients had median plasma αGAL activity 0.2 nmol/hour/mL (range: 0.0, 2.0) and median leukocyte αGAL activity 0.5 nmol/hour/mg (range: 0.0, 12.5). All 14 males had elevated plasma GL-3 levels (i.e., >7.03 µg/mL) at baseline, whereas the two females had normal plasma GL-3 levels. Median eGFR was normal (112.1 mL/min/1.73 m^2) at baseline and did not change during treatment, and median urinary protein was 151.0 mg/24 hr (range: 70.0, 431.0). All patients received FABRAZYME 1 mg/kg every two weeks for up to 48 weeks.

Study 5 was a long-term, observational study assessing the rate of decline in renal function (eGFR slope) in 122 patients with Fabry disease aged 16 years and older treated with FABRAZYME. Treated patients were matched 1:1 based on age (at FABRAZYME initiation), sex, Fabry disease subtype (classic or non-classic), and baseline eGFR to a historical cohort of untreated patients with Fabry disease. The median follow-up time was 3 years in the untreated group and 4.5 years in the treated group (maximum follow-up time 5 years in both groups). In the matched cohort, the median age (at FABRAZYME initiation) was 35 years, 72% of patients were male, 84% of patients had the classic Fabry disease subtype, and the median baseline eGFR was 93 mL/min/1.73 m^2. The estimated mean eGFR slope was -1.5 mL/min/1.73 m^2/year in the FABRAZYME-treated group and -3.2 mL/min/1.73 m^2/year in the untreated group (eGFR slope difference: 1.7 mL/min/1.73 m^2/year; 95% CI: 0.5, 3.0).

16 HOW SUPPLIED/STORAGE AND HANDLING

FABRAZYME (agalsidase beta) for injection is supplied as a sterile, nonpyrogenic, white to off-white lyophilized cake or powder in single-dose vials.

35 mg vial: NDC 58468-0040-1

5 mg vial: NDC 58468-0041-1

STORAGE AND HANDLING

Refrigerate vials of FABRAZYME at 2°C to 8°C (36°F to 46°F). Do not use FABRAZYME after the expiration date on the vial.

This product contains no preservatives. Reconstituted and diluted solutions of FABRAZYME should be used immediately. If immediate use is not possible, the reconstituted and diluted solution may be stored for up to 24 hours at 2°C to 8°C (36°F to 46°F) [see Dosage and Administration (2.2)].

17 PATIENT COUNSELING INFORMATION

Hypersensitivity Reactions Including Anaphylaxis and Infusion-Associated Reactions (IARs)

Advise the patient and caregiver that life-threatening hypersensitivity reactions, including anaphylaxis, and IARs may occur with FABRAZYME treatment.

Advise the patient or caregiver that anaphylaxis has occurred during the early course of enzyme replacement therapy and after extended duration therapy.

Inform the patient and caregiver of the symptoms of life-threatening hypersensitivity reactions, including anaphylaxis, and IARs and to seek immediate medical care should symptoms occur [see Warnings and Precautions (5.1, 5.2)].

FABRAZYME Exposure During Pregnancy or Lactation

Advise a pregnant or lactating woman exposed to FABRAZYME to report FABRAZYME exposure to her healthcare provider and by calling 1-800-633-1610, option 1 [see Use in Specific Populations (8.1., 8.2)].

Patient Registry

Inform the patient and/or caregiver that a registry has been established for Fabry patients in order to better understand the variability and progression of Fabry disease in the population as a whole, and in women along with monitoring and evaluating long-term treatment effects of FABRAZYME. Additionally, the registry also monitors the effect of FABRAZYME on pregnant women and their offspring. Encourage the patient and/or caregiver to contact the registry program by visiting www. registrynxt.com or by calling 1-800-745-4447, extension 15500.

Manufactured by:
Genzyme Corporation
450 Water Street
Cambridge, MA 02141
A SANOFI COMPANY
U.S. License Number: 1596

FABRAZYME and Genzyme are registered trademarks of Genzyme Corporation

PRINCIPAL DISPLAY PANEL - 5 mg Vial Carton

NDC 58468-0041-1
Rx only

Fabrazyme®
agalsidase beta

5 mg per vial

for Injection

For Intravenous
Infusion after Dilution

One single-dose vial
Discard unused portion

sanofi

PRINCIPAL DISPLAY PANEL - 35 mg Vial Carton

NDC 58468-0040-1
Rx only

Fabrazyme®
agalsidase beta

35 mg per vial

for Injection

For Intravenous
Infusion after Dilution

One single-dose vial
Discard unused portion

sanofi